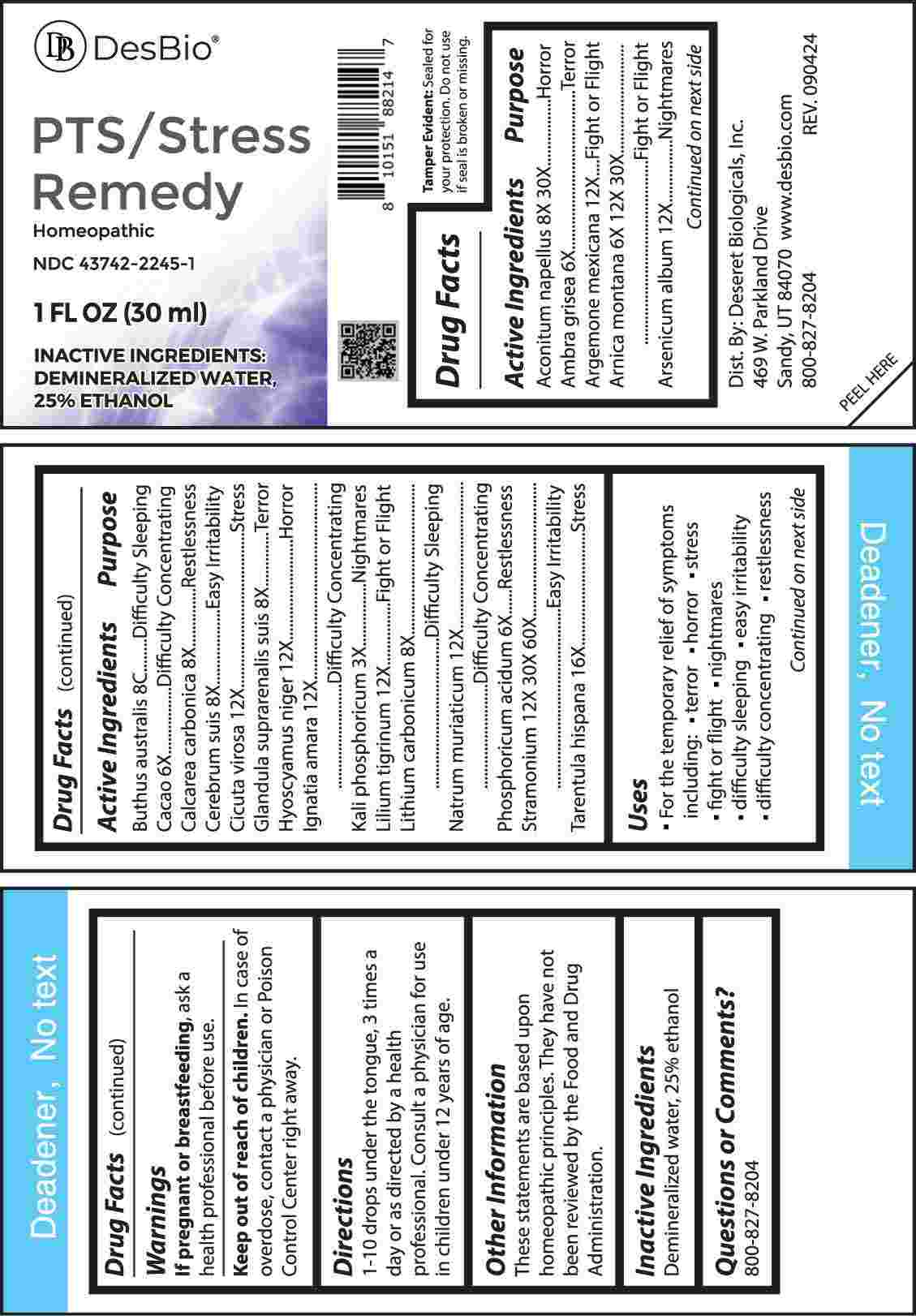 DRUG LABEL: PTS/Stress Remedy
NDC: 43742-2245 | Form: LIQUID
Manufacturer: Deseret Biologicals, Inc.
Category: homeopathic | Type: HUMAN OTC DRUG LABEL
Date: 20250120

ACTIVE INGREDIENTS: ACONITUM NAPELLUS WHOLE 8 [hp_X]/1 mL; AMBERGRIS 6 [hp_X]/1 mL; ARGEMONE MEXICANA 12 [hp_X]/1 mL; ARNICA MONTANA WHOLE 6 [hp_X]/1 mL; ARSENIC TRIOXIDE 12 [hp_X]/1 mL; ANDROCTONUS AUSTRALIS VENOM 12 [hp_X]/1 mL; COCOA 6 [hp_X]/1 mL; OYSTER SHELL CALCIUM CARBONATE, CRUDE 8 [hp_X]/1 mL; SUS SCROFA CEREBRUM 8 [hp_X]/1 mL; CICUTA VIROSA ROOT 12 [hp_X]/1 mL; SUS SCROFA ADRENAL GLAND 8 [hp_X]/1 mL; HYOSCYAMUS NIGER 12 [hp_X]/1 mL; STRYCHNOS IGNATII SEED 12 [hp_X]/1 mL; DIBASIC POTASSIUM PHOSPHATE 3 [hp_X]/1 mL; LILIUM LANCIFOLIUM WHOLE FLOWERING 12 [hp_X]/1 mL; LITHIUM CARBONATE 8 [hp_X]/1 mL; SODIUM CHLORIDE 12 [hp_X]/1 mL; PHOSPHORIC ACID 6 [hp_X]/1 mL; DATURA STRAMONIUM 12 [hp_X]/1 mL; LYCOSA TARANTULA 16 [hp_X]/1 mL
INACTIVE INGREDIENTS: WATER; ALCOHOL

DRUG FACTS:

ACTIVE INGREDIENTS:

Aconitum Napellus 8X, 30X, Ambra Grisea 6X, Argemone Mexicana 12X, Arnica Montana 6X, 12X, 30X, Arsenicum Album 12X, Buthus Australis 8C, Cacao 6X, Calcarea Carbonica 8X, Cerebrum Suis 8X, Cicuta Virosa 12X, Glandula Suprarenalis Suis 8X, Hyoscyamus Niger 12X, Ignatia Amara 12X, Kali Phosphoricum 3X, Lilium Tigrinum 12X, Lithium Carbonicum 8X, Natrum Muriaticum 12X, Phosphoricum Acidum 6X, Stramonium 12X, 30X, 60X, Tarentula Hispana 16X.

PURPOSE:

Aconitum Napellus - Horror, Ambra Grisea - Terror, Argemone Mexicana – Fight or Flight, Arnica Montana – Fight or Flight, Arsenicum Album - Nightmares, Buthus Australis – Difficulty Sleeping, Cacao – Difficulty Concentrating, Calcarea Carbonica - Restlessness, Cerebrum Suis – Easy Irritability, Cicuta Virosa - Stress, Glandula Suprarenalis Suis - Terror, Hyoscyamus Niger - Horror, Ignatia Amara – Difficulty Concentrating, Kali Phosphoricum - Nightmares, Lilium Tigrinum – Fight or Flight, Lithium Carbonicum – Difficulty Sleeping, Natrum Muriaticum – Difficulty Concentrating, Phosphoricum Acidum - Restlessness, Stramonium – Easy Irritability, Tarentula Hispana - Stress

USES:

• For the temporary relief of symptoms including:

• terror • horror • stress • fight or flight • nightmares

• difficulty sleeping • easy irritability • difficulty concentrating • restlessness

These statements are based upon homeopathic principles. They have not been reviewed by the Food and Drug Administration.

WARNINGS:

If pregnant or breastfeeding, ask a health professional before use.

Keep out of reach of children. In case of overdose, contact a physician or Poison Control Center right away.

Tamper Evident: Sealed for your protection. Do not use if seal is broken or missing.

KEEP OUT OF REACH OF CHILDREN:

In case of overdose, contact a physician or Poison Control Center right away.

DIRECTIONS:

1-10 drops under the tongue, 3 times a day or as directed by a health professional. Consult a physician for use in children under 12 years of age.

INACTIVE INGREDIENTS:

Demineralized water, 25% ethanol

QUESTIONS:

Dist. By: Deseret Biologicals, Inc.

469 W. Parkland Drive

Sandy, UT 84070

www.desbio.com

800-827-8204

PACKAGE LABEL DISPLAY:

DesBio

PTS/Stress

Remedy

Homeopathic

NDC 43742-2245-1

1 FL OZ (30 ml)